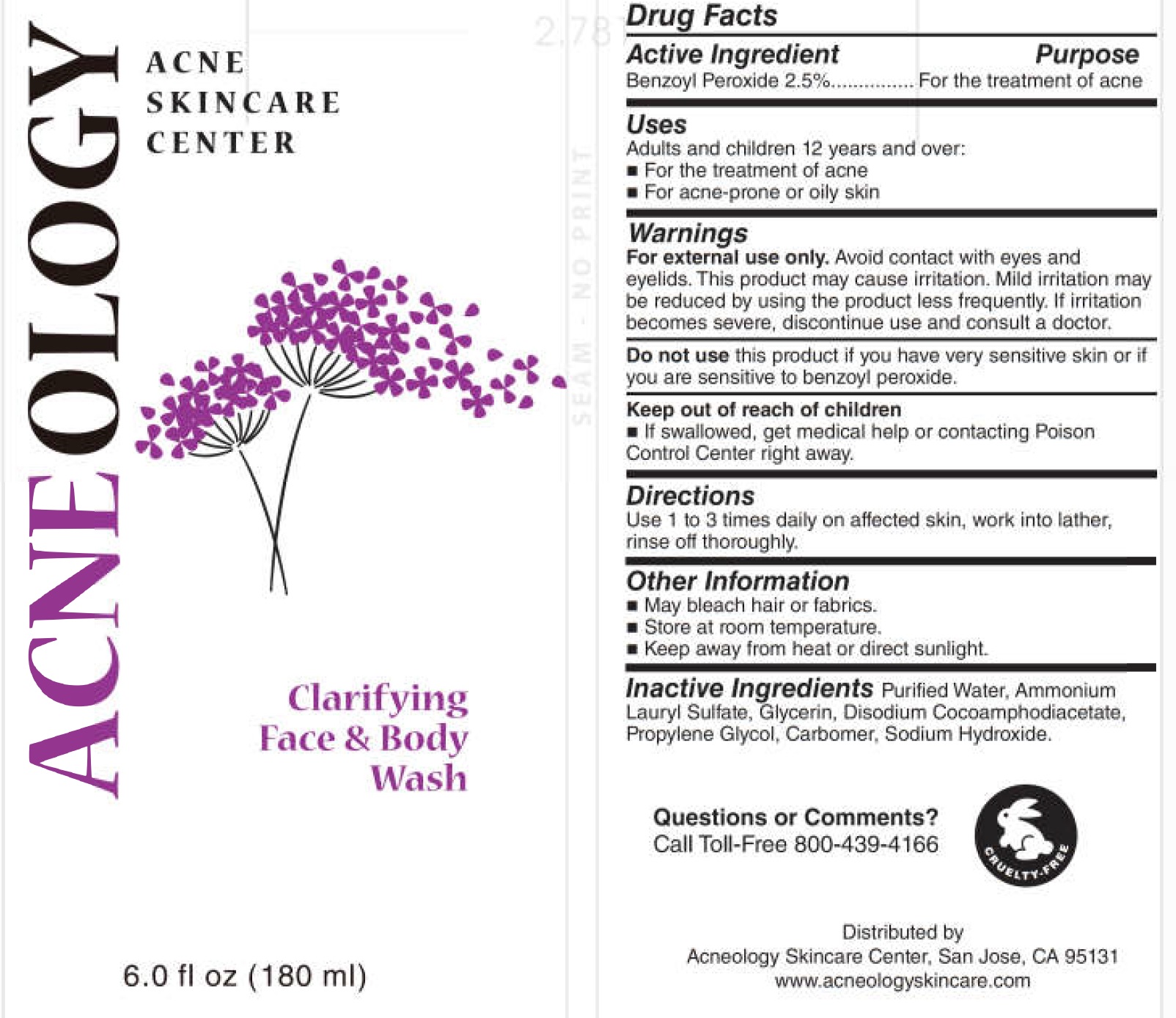 DRUG LABEL: Clarifying Face and Body Wash
NDC: 73610-000 | Form: LIQUID
Manufacturer: Acneology Treatment Center, LLC
Category: otc | Type: HUMAN OTC DRUG LABEL
Date: 20210924

ACTIVE INGREDIENTS: BENZOYL PEROXIDE 25 mg/1 mL
INACTIVE INGREDIENTS: WATER; AMMONIUM LAURYL SULFATE; GLYCERIN; DISODIUM COCOAMPHODIACETATE; PROPYLENE GLYCOL; CARBOMER HOMOPOLYMER, UNSPECIFIED TYPE; SODIUM HYDROXIDE

Clarifying Face & Body Wash

Active Ingredient

Benzoyl Peroxide 2.5%

Purpose

For the treatment of acne

Uses

Adults and children 12 years and over:

- For the treatment of acne
- For acne-prone or oily skin

Warnings

For external use only. Avoid contact with eyes and eyelids. This product may cause irritation. Mild irritation may be reduced by using the product less frequently. If irritation becomes severe, discontinue use and consult a doctor.

Do not use

this product if you have very sensitive skin or if you are sensitive to benzoyl peroxide.

Keep out of reach of children

- If swallowed, get medical help or contacting Poison Control Center right away.

Directions

Use 1 to 3 times daily on affected skin, work into lather, rinse off thoroughly.

Other Information

- May bleach hair or fabrics.
- Store at room temperature.
- Keep away from heat or direct sunlight.

Inactive Ingredients

Purified Water, Ammonium Lauryl Sulfate, Glycerin, Disodium Cocoamphodiacetate, Propylene Glycol, Carbomer, Sodium Hydroxide.

Questions or Comments?

Call Toll-Free 800-439-4166